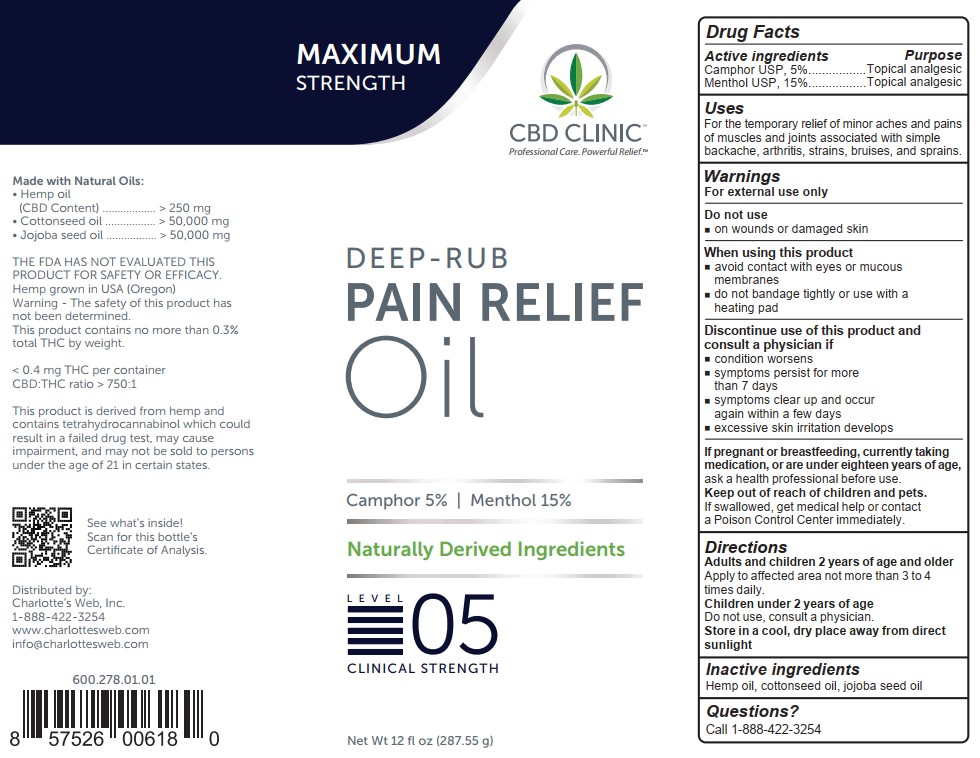 DRUG LABEL: CBD Clinic Deep-Rub Pain Relief - Level 5
NDC: 73096-754 | Form: OIL
Manufacturer: ABACUS HEALTH PRODUCTS, INC.
Category: otc | Type: HUMAN OTC DRUG LABEL
Date: 20250114

ACTIVE INGREDIENTS: CAMPHOR (NATURAL) 5 g/100 g; MENTHOL 15 g/100 g
INACTIVE INGREDIENTS: COTTONSEED OIL; HEMP; JOJOBA OIL

CBD Clinic Deep-Rub Pain Relief Oil - Level 5

Active ingredients

Camphor USP, 5%

Menthol USP, 15%

Purpose

Camphor USP, 5%....................Topical analgesic

Menthol USP, 15%....................Topical analgesic

Uses

For the temporary relief of minor aches and pains of muscles and joints associated with simple backache, arthritis, strains, bruises, and sprains.

Warnings

Do not use

- on wounds or damaged skin

When using this product

- avoid contact with eyes or mucous membranes
- do not bandage tightly or use with a heating pad

STOP USE

Discontinue use of this product and consult a physician if

- condition worsens
- symptoms persist for more than 7 days
- symptoms clear up and occur again within a few days
- excessive skin irritation develops

PREGNANCY OR BREAST FEEDING

If pregnant or breastfeeding, currently taking medication, or are under eighteen years of age,ask a health professional before use.

Keep out of reach of children and pets.If swallowed, get medical help or contact a Poison Control Center immediately.

Directions

Adults and children 2 years of age and older

Apply to affected area not more than 3 to 4 times daily.

Children under 2 years of age

Do not use, consult a physician.

Store in a cool, dry place away from direct sunlight

Inactive ingredients

Hemp oil, cottonseed oil, jojoba seed oil

Questions?

Call 1-888-422-3254

PACKAGE LABEL

Maximum Strength

CBD Clinic

Professional Care. Powerful Relief.

Deep-Rub

Pain Relief

Oil

Camphor 5% | Menthol 15%

Naturally Derived Ingredients

Level 05

Clinical Strength

Net Wt 12 fl oz (287.55 g)